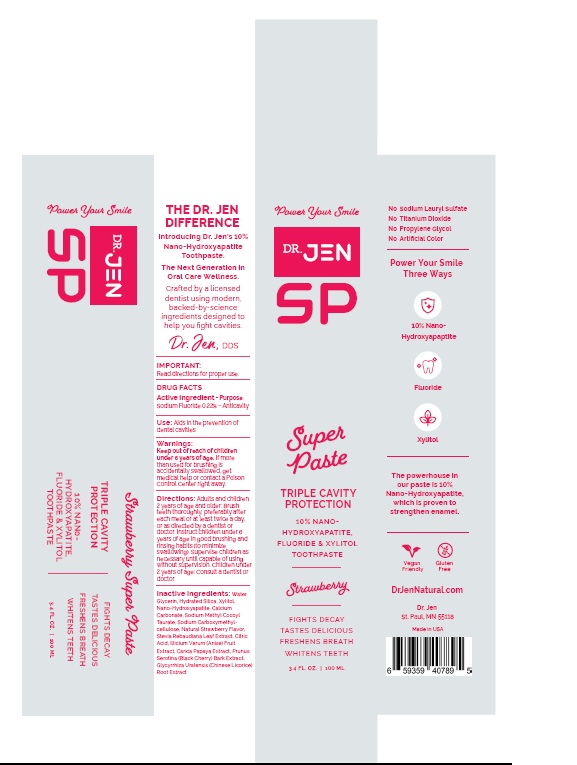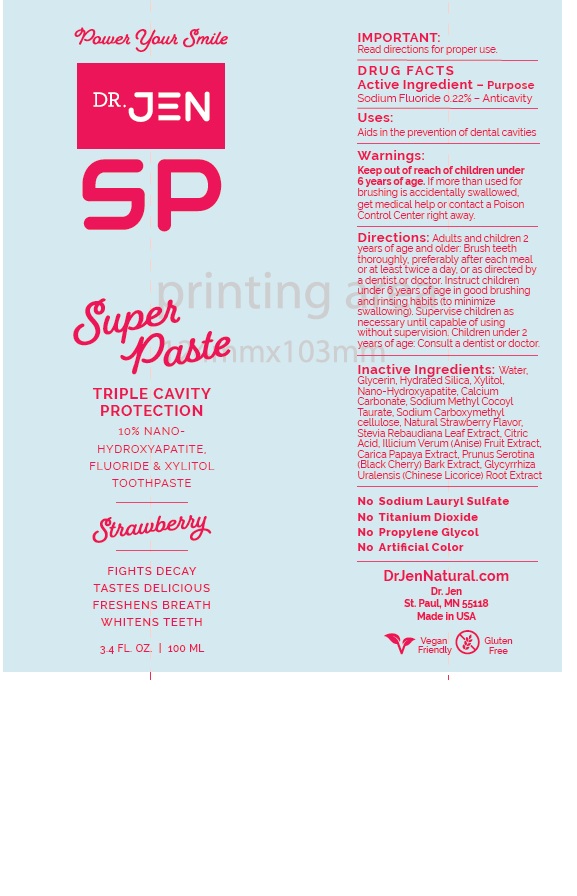 DRUG LABEL: Dr. Jen SuperPaste Nano-Hydroxyapatite
NDC: 84181-735 | Form: PASTE, DENTIFRICE
Manufacturer: Dr Jen Natural, LLC
Category: otc | Type: HUMAN OTC DRUG LABEL
Date: 20251205

ACTIVE INGREDIENTS: SODIUM FLUORIDE 0.22 g/100 mL
INACTIVE INGREDIENTS: WATER; GLYCERIN; HYDRATED SILICA; XYLITOL; TRIBASIC CALCIUM PHOSPHATE; CALCIUM CARBONATE; SODIUM METHYL COCOYL TAURATE; CARBOXYMETHYLCELLULOSE SODIUM, UNSPECIFIED; STEVIA REBAUDIUNA LEAF; CITRIC ACID MONOHYDRATE; STAR ANISE FRUIT; CARICA PAPAYA LEAF; PRUNUS SEROTINA BARK; GLYCYRRHIZA URALENSIS ROOT

Dr. Jen SuperPaste Nano-Hydroxyapatite + Fluoride Toothpaste

DRUG FACTS

Active Ingredient
Sodium Fluoride 0.22%

Purpose:
Sodium Fluoride - Anticavity

INDICATIONS AND USAGE

Use: Aids in the prevention of dental cavities

Warnings:

If more than used for brushing is
accidentally swallowed, get
medical help or contact a Poison
Control Center right away.

Keep out of reach of children
under 6 years of age.

DOSAGE AND ADMINISTRATION

Directions: Adults and children
2 years of age and older: Brush
teeth thoroughly, preferably after
each meal or at least twice a day,
or as directed by a dentist or
doctor. Instruct children under 6
years of age in good brushing and
rinsing habits (to minimize
swallowing). Supervise children as
necessary until capable of using
without supervision. Children under
2 years of age: Consult a dentist or
doctor.

Inactive Ingredients: Water,
Glycerin, Hydrated Silica, Xylitol,
Nano-Hydroxyapatite, Calcium
Carbonate, Sodium Methyl Cocoyl
Taurate, Sodium Carboxymethyl-
cellulose, Natural Strawberry Flavor,
Stevia Rebaudiana Leaf Extract, Citric
Acid, Illicium Verum (Anise) Fruit
Extract, Carica Papaya Extract, Prunus
Serotina (Black Cherry) Bark Extract,
Glycyrrhiza Uralensis (Chinese Licorice)
Root Extract

Dr. Jen SuperPaste Product Package Labeling

Dr. Jen

Super Paste

TRIPLE CAVITY
PROTECTION

10% NANO-HYDROXYAPATITE,
FLUORIDE & XYLITOL
TOOTHPASTE

Strawberry

3.4 FL. OZ. | 100 ML

DrJenNatural.com

Dr. Jen
St. Paul, MN 55118

res